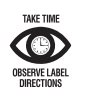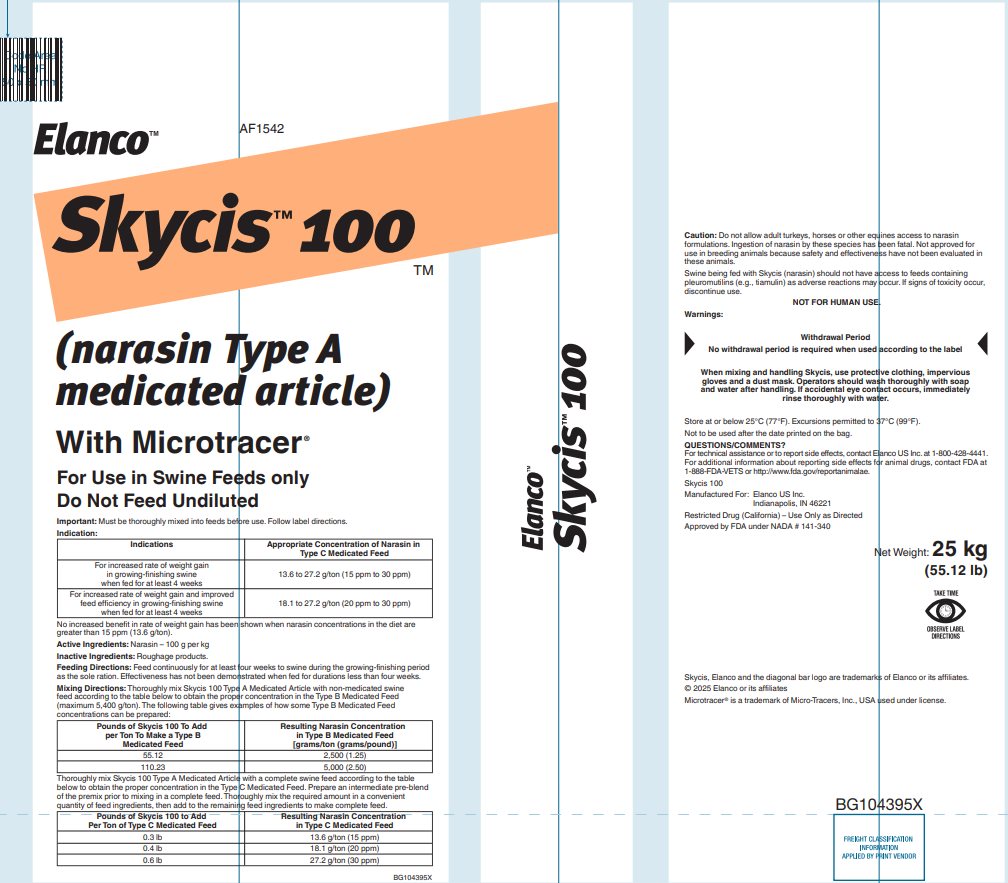 DRUG LABEL: Skycis
NDC: 58198-1542 | Form: GRANULE
Manufacturer: Elanco US Inc.
Category: animal | Type: OTC TYPE A MEDICATED ARTICLE ANIMAL DRUG LABEL
Date: 20260121

ACTIVE INGREDIENTS: narasin 100 g/1 kg

Elanco™

AF1542

Skycis™ 100

(narasin Type A medicated article)

With Microtracer®

For Use in Swine Feeds only

Do Not Feed Undiluted

Important: Must be thoroughly mixed into feeds before use. Follow label directions.

Indication:

Indications | Appropriate Concentration of Narasin in Type C Medicated Feed
For increased rate of weight gain in growing-finishing swine when fed for at least 4 weeks | 13.6 to 27.2 g/ton (15 ppm to 30 ppm)
For increased rate of weight gain and improved feed efficiency in growing-finishing swine when fed for at least 4 weeks | 18.1 to 27.2 g/ton (20 ppm to 30 ppm)

No increased benefit in rate of weight gain has been shown when narasin concentrations in the diet are greater than 15 ppm (13.6 g/ton).

Active Ingredients: Narasin – 100 g per kg

Inactive Ingredients: Roughage products.

Feeding Directions: Feed continuously for at least four weeks to swine during the growing-finishing period as the sole ration. Effectiveness has not been demonstrated when fed for durations less than four weeks.

Mixing Directions: Thoroughly mix Skycis 100 Type A Medicated Article with non-medicated swine feed according to the table below to obtain the proper concentration in the Type B Medicated Feed (maximum 5,400 g/ton). The following table gives examples of how some Type B Medicated Feed concentrations can be prepared:

Pounds of Skycis 100 To Add per Ton To Make a Type B Medicated Feed | Resulting Narasin Concentration in Type B Medicated Feed [grams/ton (grams/pound)]
55.12 | 2,500 (1.25)
110.23 | 5,000 (2.50)

Thoroughly mix Skycis 100 Type A Medicated Article with a complete swine feed according to the table below to obtain the proper concentration in the Type C Medicated Feed. Prepare an intermediate pre-blend of the premix prior to mixing in a complete feed. Thoroughly mix the required amount in a convenient quantity of feed ingredients, then add to the remaining feed ingredients to make complete feed.

Pounds of Skycis 100 to Add Per Ton of Type C Medicated Feed | Resulting Narasin Concentration in Type C Medicated Feed
0.3 lb | 13.6 g/ton (15 ppm)
0.4 lb | 18.1 g/ton (20 ppm)
0.6 lb | 27.2 g/ton (30 ppm)

Caution: Do not allow adult turkeys, horses or other equines access to narasin formulations. Ingestion of narasin by these species has been fatal. Not approved for use in breeding animals because safety and effectiveness have not been evaluated in these animals.

Swine being fed with Skycis (narasin) should not have access to feeds containing pleuromutilins (e.g., tiamulin) as adverse reactions may occur. If signs of toxicity occur, discontinue use.

NOT FOR HUMAN USE.

Warnings:

Withdrawal Period

No withdrawal period is required when used according to the label

When mixing and handling Skycis, use protective clothing, impervious
gloves and a dust mask. Operators should wash thoroughly with soap
and water after handling. If accidental eye contact occurs, immediately
rinse thoroughly with water.

Store at or below 25°C (77°F). Excursions permitted to 37°C (99°F).

Not to be used after the date printed on the bag.

QUESTIONS/COMMENTS?

For technical assistance or to report side effects, contact Elanco US Inc. at 1-800-428-4441.

For additional information about reporting side effects for animal drugs, contact FDA at 1-888-FDA-VETS or http://www.fda.gov/reportanimalae.

Skycis 100

Manufactured For: Elanco US Inc.

Indianapolis, IN 46221

Restricted Drug (California) – Use Only as Directed

Approved by FDA under NADA # 141-340

Net Weight: 25 kg

(55.12 lb)

Skycis, Elanco and the diagonal bar logo are trademarks of Elanco or its affiliates.

© 2025 Elanco or its affiliates

Microtracer® is a trademark of Micro-Tracers, Inc., USA used under license.

BG104395X

Principal Display Panel - 25 kg Bag Label

Elanco™

AF1542

Skycis™ 100

(narasin Type A
medicated article)

With Microtracer®

For Use in Swine Feeds only

Do Not Feed Undiluted